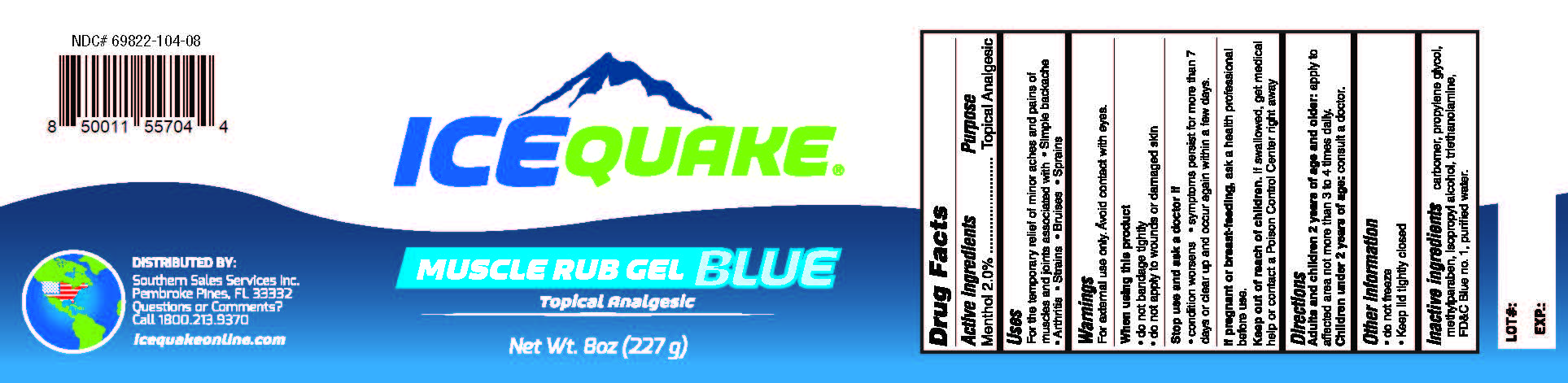 DRUG LABEL: Ice Quake Muscle Rub Blue
NDC: 69822-104 | Form: GEL
Manufacturer: Southern Sales & Service, Inc.
Category: otc | Type: HUMAN OTC DRUG LABEL
Date: 20231129

ACTIVE INGREDIENTS: MENTHOL 0.02 g/1 g
INACTIVE INGREDIENTS: CARBOMER HOMOPOLYMER, UNSPECIFIED TYPE; PROPYLENE GLYCOL; METHYLPARABEN; ISOPROPYL ALCOHOL; TROLAMINE; FD&C BLUE NO. 1; WATER

IceQuake Muscle Rub Blue

Active ingredients

Menthol 2.0%

Purpoose

Topical Analgesic

Uses

For the temporary relief of minor aches and pains of muscles and joints associated with

- simple backache
- arthritis
- strains
- bruises
- sprains

Warnings

For external use only. Avoid contact with eyes.

When using this product

- do not bandage tightly
- do not apply to wounds or damaged skin

Stop use and ask a doctor if

- condition worsens
- symptoms persist for more than 7 days or clear up and occur again within a few days.

If pregnant or breast-feeing,

ask a health professional before use.

Keep out of reach of children.

If swallowed, get medical help or contact a Poison Control Center right away.

Directions

apply to affected area not more than 3 to 4 times daily. Adults and children 2 years of age and older:

consult a doctor. Children under 2 years of age:

Other information

- do not freeze
- Keep lid tightly closed

Inactive ingredients

carbomer, propylene glycol, methylparaben, isopropyl alcohol, triethanolamine, FD&C Blue #1, purified water.